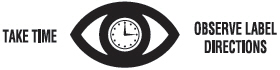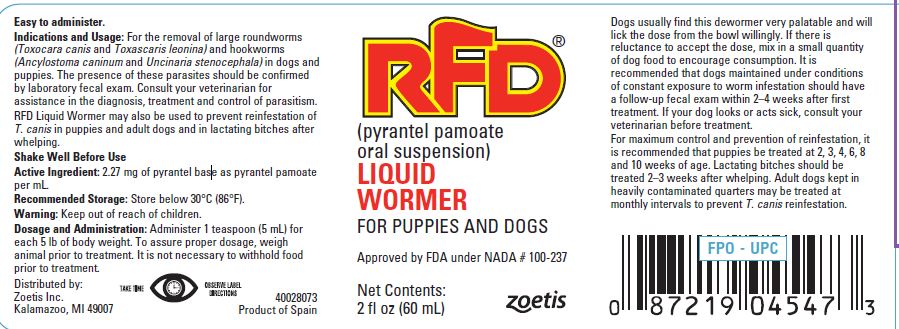 DRUG LABEL: RFD Wormer
NDC: 54771-2407 | Form: SUSPENSION
Manufacturer: Zoetis Inc.
Category: animal | Type: OTC ANIMAL DRUG LABEL
Date: 20200506

ACTIVE INGREDIENTS: pyrantel pamoate 2.27 mg/1 mL

RFD®

RFD®
(pyrantel pamoate oral suspension)

LIQUID WORMER
FOR PUPPIES AND DOGS

Approved by FDA under NADA # 100-237

Net Contents:
2 fl oz (60 mL)

Easy to administer.

Indications and Usage

For the removal of large roundworms (Toxocara canis and Toxascaris leonina) and hookworms (Ancylostoma caninum and Uncinaria stenocephala) in dogs and puppies. The presence of these parasites should be confirmed by laboratory fecal exam. Consult your veterinarian for assistance in the diagnosis, treatment and control of parasitism.

RFD Liquid Wormer may also be used to prevent reinfestation of T. canis in puppies and adult dogs and in lactating bitches after whelping.

Dogs usually find this dewormer very palatable and will lick the dose from the bowl willingly. If there is reluctance to accept the dose, mix in a small quantity of dog food to encourage consumption. It is recommended that dogs maintained under conditions of constant exposure to worm infestation should have a follow-up fecal exam within 2–4 weeks after first treatment. If your dog looks or acts sick, consult your veterinarian before treatment.
For maximum control and prevention of reinfestation, it is recommended that puppies be treated at 2, 3, 4, 6, 8 and 10 weeks of age. Lactating bitches should be treated 2–3 weeks after whelping. Adult dogs kept in heavily contaminated quarters may be treated at monthly intervals to prevent T. canis reinfestation.

Shake Well Before Use

Active Ingredient

2.27 mg of pyrantel base as pyrantel pamoate per mL.

Recommended Storage

Store below 30°C (86°F).

Warning

Keep out of reach of children.

Dosage and Administration

Administer 1 teaspoon (5 mL) for each 5 lb of body weight. To assure proper dosage, weigh animal prior to treatment. It is not necessary to withhold food prior to treatment.

Distributed by:
Zoetis Inc.
Kalamazoo, MI 49007

40028073
Product of Spain